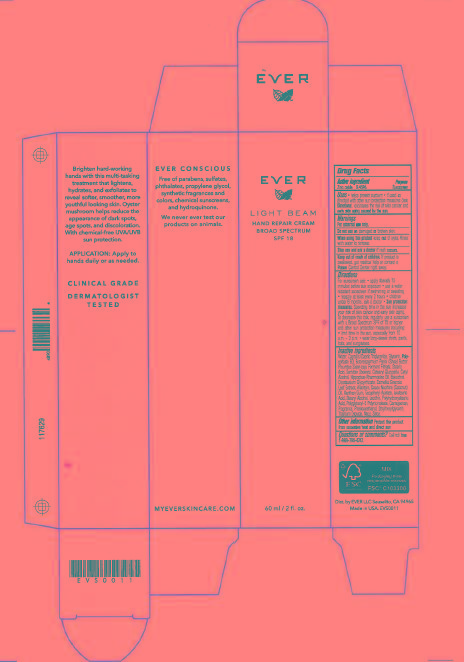 DRUG LABEL: Light Beam Hand Repair Cream Broad Spectrum SPF 18
NDC: 62742-4082 | Form: CREAM
Manufacturer: Allure Labs, Inc
Category: otc | Type: HUMAN OTC DRUG LABEL
Date: 20160428

ACTIVE INGREDIENTS: ZINC OXIDE 9.45 mg/1 mL
INACTIVE INGREDIENTS: WATER; MEDIUM-CHAIN TRIGLYCERIDES; GLYCERIN; POLYSORBATE 60; SHEA BUTTER; STEARIC ACID; SORBITAN MONOSTEARATE; CETEARYL GLUCOSIDE; CETYL ALCOHOL; HIPPOPHAE RHAMNOIDES FRUIT OIL; BAKUCHIOL; GLYCYRRHIZINATE DIPOTASSIUM; GREEN TEA LEAF; ALLANTOIN; COCONUT OIL; XANTHAN GUM; .ALPHA.-TOCOPHEROL ACETATE; ISOSTEARIC ACID; STEARYL ALCOHOL; EGG PHOSPHOLIPIDS; POLYHYDROXYSTEARIC ACID (2300 MW); POLYGLYCERYL-3 RICINOLEATE; CARRAGEENAN; PHENOXYETHANOL; ETHYLHEXYLGLYCERIN; TITANIUM DIOXIDE; MICA; SILICON DIOXIDE

DRUG FACTS

Active Ingredient: Zinc Oxide - 9.45%

Purpose: Sunscreen

Uses:

- Helps prevent sunburn.
- If used as directed with other sun protection measures, decreases the risk of skin cancer and early skin aging caused by the sun.

Warnings: For external use only.

Do not use on:

- Damaged or broken skin.

When using this product:

- Keep out of eyes.
- Rinse with water to remove.

Stop use and ask a doctor:

- If rash occurs.

Keep out of reach of children. If product is swallowed, get medical help or contact a Poison Control Center right away.

DOSAGE AND ADMINISTRATION

For sunscreen use:

- Apply liberally 15 minutes before sun exposer.
- Use a water resistant sunscreen if swimming or sweating.
- Reapply at least every 2 hours.
- Children under 6 months: ask a doctor.
- Sun protection measures. Spending time in the sun increases your risk of skin cancer and early skin aging. To decrease this risk, regularly use a sunscreen with a Broad Spectrum SPF of 15 or higher and other sun protection measures including:
- Limit time in the sun, especially from 10 a.m. - 2 p.m.
- Wear long sleeve shirts, pants, hats and sunglasses.

INACTIVE INGREDIENT

Water, Caprylic/Capric Triglycerides, Glycerin, Polysorbate 60, Butyrospermum Parkii (Shea) Butter, Pleurotus Sajor-caju Ferment Filtrate, Stearic Acid, Sorbitan Stearate, Cetearyl Glucoside, Cetyl Alcohol, Hippophae Rhamnoides oil, Bakuchiol, Dipotassium Glycyrrhizate, Camellia Sinensis Leaf Extract, Allantoin, Cross Nucifera (Cococnut) Oil, Xanthan Gum, Tocopheryl Acetate, Isostearic Acid, Stearyl Alcohol, Lecithin, Polyhydroxystearic Acid, Polyglyceryl-3 Ricinoleate, Carrageenan, Fragrance, Phenoxyethanol, Ethylhexylglycerin, Titanium Dioxide, Mica, Silica.

STORAGE AND HANDLING

Protect this product from excessive heat and direct sun.

PACKAGE LABEL

Dist. by: EVER LLC Sausalito, CA 94965